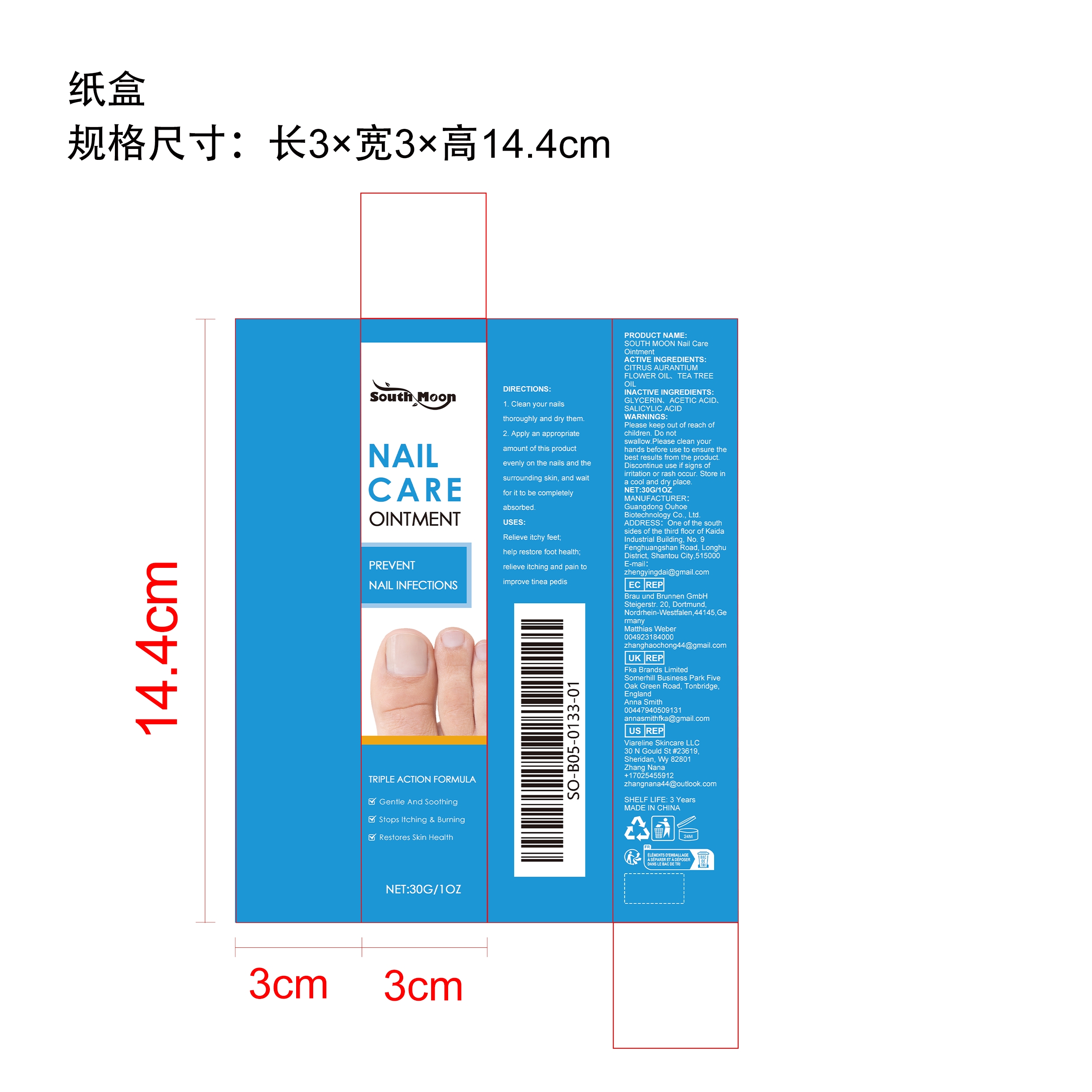 DRUG LABEL: SOUTH MOON Nail Care
NDC: 84744-060 | Form: CREAM
Manufacturer: Guangdong Ouhoe Biotechnology Co., Ltd.
Category: otc | Type: HUMAN OTC DRUG LABEL
Date: 20241024

ACTIVE INGREDIENTS: CITRUS AURANTIUM FLOWER OIL 9 g/30 g; TEA TREE OIL 3 g/30 g
INACTIVE INGREDIENTS: SALICYLIC ACID 9 g/30 g; GLYCERIN 4.5 g/30 g; (2-NAPHTHYLOXY)ACETIC ACID 4.5 g/30 g

ACTIVE INGREDIENTS

CITRUS AURANTIUM FLOWER OIL,TEA TREE OIL

purpose

Relieve itchy feet;help restore foot health;relieve itching and pain toimprove tinea pedis

use

1. Clean your nailsthoroughly and dry them.

2. Apply an appropriateamount of this productevenly on the nails and thesurrounding skin, and waitfor it to be completelyabsorbed.

WARNINGS

Please keep out of reach of children. Do not swallow. Please clean your hands before use to ensure the best results from the product. Discontinue use if signs of irritation or rash occur. Store in a cool and dry place.

KEEP OUT OF REACH OF CHILDREN

Please keep out of reach of children. Do not swallow.

stop use

Discontinue use if signs of irritation or rash occur.

Do not use

Discontinue use if signs of irritation or rash occur.

STORAGE AND HANDLING

Store in a cool and dry place.

INACTIVE INGREDIENT

GLYCERIN、ACETIC ACID、SALICYLIC ACID